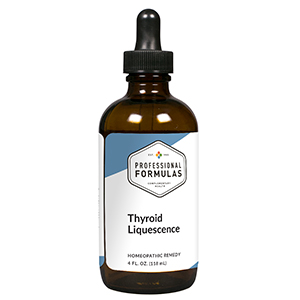 DRUG LABEL: Thyroid Liquescence
NDC: 63083-3021 | Form: LIQUID
Manufacturer: Professional Complementary Health Formulas
Category: homeopathic | Type: HUMAN OTC DRUG LABEL
Date: 20190815

ACTIVE INGREDIENTS: FUCUS VESICULOSUS 4 [hp_X]/118 mL; IODINE 4 [hp_X]/118 mL; SPONGIA OFFICINALIS SKELETON, ROASTED 4 [hp_X]/118 mL; SKIM MILK 6 [hp_X]/118 mL; MOLYBDENUM 6 [hp_X]/118 mL; ENTEROBIUS VERMICULARIS 6 [hp_X]/118 mL; THYROID, UNSPECIFIED 6 [hp_X]/118 mL; CALCIUM HEXAFLUOROSILICATE 8 [hp_X]/118 mL; REDUCTIC ACID 8 [hp_X]/118 mL
INACTIVE INGREDIENTS: ALCOHOL; WATER

T21

ACTIVE INGREDIENTS

Fucus vesiculosus 4X
Iodium 4X
Spongia tosta 4X
Lac defloratum 6X
Molybdenum 6X
Parathyroid 6X
Thyroidinum 6X, 12X
Lapis albus 8X
Rutinic acidum 8X

QUESTIONS

Professional Formulas

PO Box 2034 Lake Oswego, OR 97035

INDICATIONS

For the temporary relief of fatigue, cold sensitivity, constipation, dry skin, weight gain, lethargy, or irritability.*

PURPOSE

*Claims based on traditional homeopathic practice, not accepted medical evidence. Not FDA evaluated.

WARNINGS

Consult a doctor if condition worsens or if symptoms persist. Keep out of the reach of children. In case of overdose, get medical help or contact a poison control center right away. If pregnant or breastfeeding, ask a healthcare professional before use.

Keep out of the reach of children.

PREGNANCY OR BREAST FEEDING

If pregnant or breastfeeding, ask a healthcare professional before use.

DIRECTIONS

Place drops under tongue 30 minutes before/after meals. Adults and children 12 years and over: Take one full dropper up to 2 times per day. Consult a physician for use in children under 12 years of age.

OTHER INFORMATION

Tamper resistant. If seal is broken, do not use. After opening, close container tightly and store at room temperature away from heat.

INACTIVE INGREDIENTS

20% ethanol, purified water.

LABEL

Est 1985

Professional Formulas

Complementary Health

Thyroid Liquescence

Homeopathic Remedy

4 FL. OZ. (118 mL)